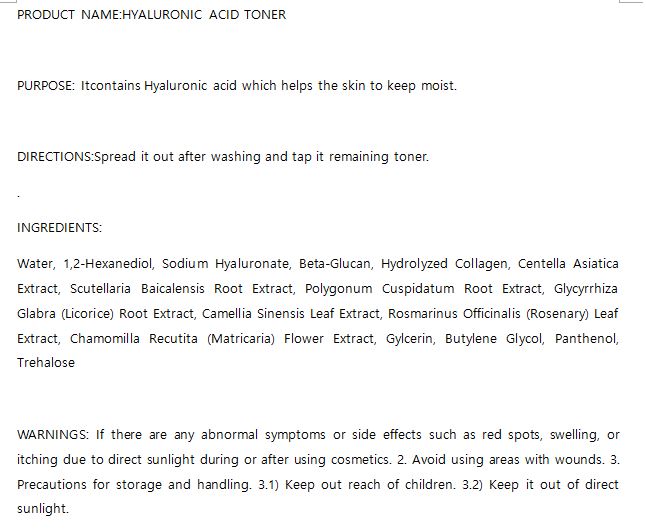 DRUG LABEL: W.SKIN HYALURONIC TONER
NDC: 74997-0019 | Form: LIQUID
Manufacturer: J&J COMPANY
Category: otc | Type: HUMAN OTC DRUG LABEL
Date: 20210508

ACTIVE INGREDIENTS: HYALURONATE SODIUM 0.5 g/100 mL
INACTIVE INGREDIENTS: GLYCERIN; WATER

J&J COMPANY - STOP-AGING PEPTIDE TONER

ACTIVE INGREDIENT

Ethylhexyl Methoxycinnamate

INACTIVE INGREDIENT

Isoamyl p-Methoxycinnamate, Bis-Ethylhexyloxyphenol Methoxyphenyl Triazine, Zinc Oxide, Propylene Glycol, Glycerin, Sodium Hyaluronate, Glyceryl Stearate, Glyceryl Stearate SE, Sorbitan Stearate, Sorbitan Sesquioleate, 1,2-Hexanediol, Polysorbate 60, Isopropyl Myristate, Caprylic/Capric Triglyceride, Cyclomethicone, Phenyl Trimethicone, C12-15 Alkyl Benzoate, Cetearyl Alcohol, Adenosine, Beeswax

PURPOSE

It has a strong sun block and waterproof function. It contains a large amount of hyaluronic acid to prevent evaporation of moisture from the skin.

keep out of reach of the children

INDICATIONS AND USAGE

At the end of skin care, take an appropriate amount and apply evenly over the skin

WARNINGS

If there are any abnormal symptoms or side effects such as red spots, swelling, or itching due to direct sunlight during or after using cosmetics. 2. Avoid using areas with wounds. 3. Precautions for storage and handling. 3.1) Keep out reach of children. 3.2) Keep it out of direct sunlight.

DOSAGE AND ADMINISTRATION

for external use only